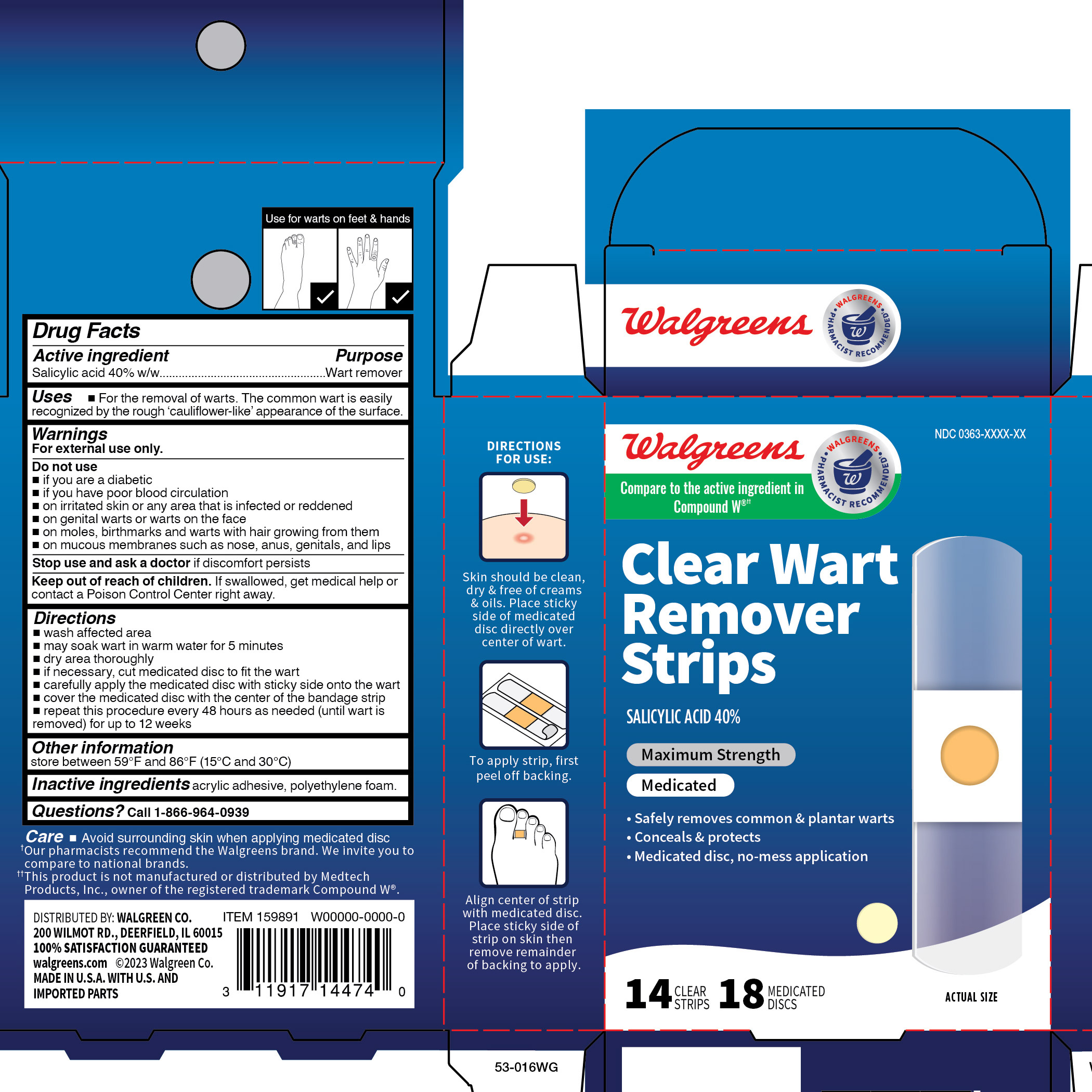 DRUG LABEL: Salicylic Acid
NDC: 0363-1747 | Form: PATCH
Manufacturer: Walgreens Company
Category: otc | Type: HUMAN OTC DRUG LABEL
Date: 20260120

ACTIVE INGREDIENTS: SALICYLIC ACID 40 mg/12 1
INACTIVE INGREDIENTS: HIGH DENSITY POLYETHYLENE

Walgreens Clear Medicated Wart Remover

Active ingredient

Salicylic acid 40% w/w

Purpose

Wart remover

Use

- For the removal of warts. The common wart is easily recognized by the rough 'cauliflower-like' appearance of the surface.

Warnings

For external use only.

Do not use

- if you are a diabetic
- if you have poor blood circulation
- on irritated skin or any area that is infected or reddened
- on genital warts or warts on the face
- on moles, birthmarks and warts with hair growing from them
- on mucous membranes such as nose, anus, genitals and lips

Stop use and ask a doctor if

discomfort persists

Keep out of reach of children.

If swallowed, get medical help or contact a Poison Control Center right away.

Directions

- wash affected area.
- may soak wart in warm water for 5 minutes.
- dry area thoroughly
- if necessary, cut medicated disc to fit the wart.
- carefully apply the medicated disc with sticky side onto the wart.
- cover the medicated disc with the center of the bandage strip.
- repeat this procedure every 48 hours as needed (until wart is removed) for up to 12 weeks.

Other information

store between 59° and 86°F (15° and 30°C)

Inactive ingredients

acrylic adhesive, polyethylene foam.

Questions?

Call 1-866-964-0939

Principal Display Panel

Walgreens

Clear Wart

Remover

Strips

SALICYLIC ACID 40%

Maximum Strength

Medicated

- Safely removes common & plantar warts
- Conceals & protects
- Medicated disc, no-mess application

14 CLEAR STRIPS 18 MEDICATED DISCS